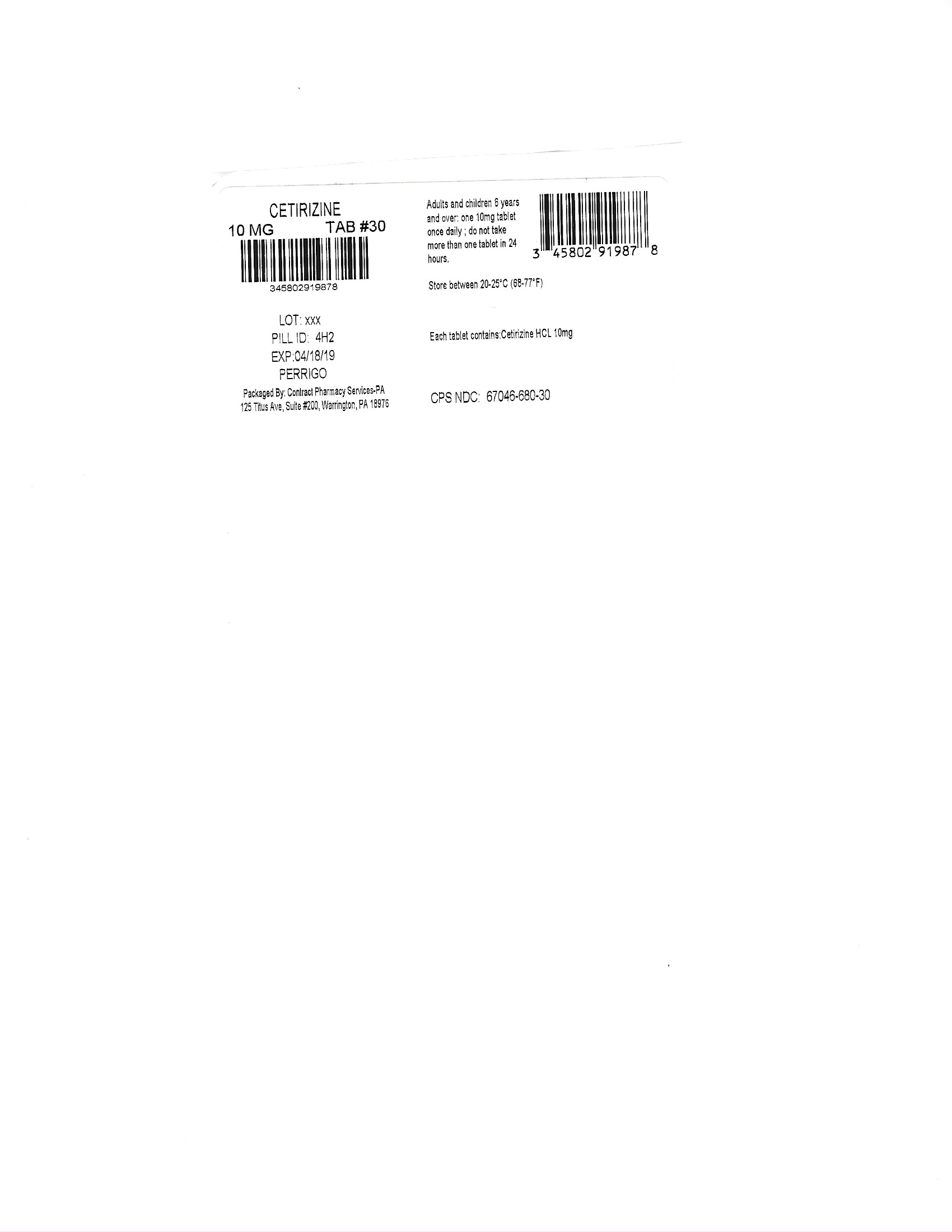 DRUG LABEL: Cetirizine
NDC: 67046-680 | Form: TABLET
Manufacturer: Contract Pharmacy Services-PA
Category: otc | Type: HUMAN OTC DRUG LABEL
Date: 20180422

ACTIVE INGREDIENTS: CETIRIZINE HYDROCHLORIDE 10 mg/1 1
INACTIVE INGREDIENTS: STARCH, CORN

HIGHLIGHTS OF PRESCRIBING INFORMATION

Cetirizine 10mg 680
"These highlights do not include all the information needed to use" "see full prescribing information for" "Initial U.S. Approval"

DOSAGE AND ADMINISTRATION

adults and children 6 years and over

one 10 mg tablet once daily; do not take more than one 10 mg tablet in 24 hours. A 5 mg product may be appropriate for less severe symptoms.

adults 65 years and over

ask a doctor

children under 6 years of age

ask a doctor

consumers with liver or kidney disease

ask a doctor

INDICATIONS AND USAGE

temporarily relieves these symptoms due to hay fever or other upper respiratory allergies:

•
runny nose
•
sneezing
•
itchy, watery eyes
•
itching of the nose or throat

FULL PRESCRIBING INFORMATION

ACTIVE INGREDIENT

Cetirizine HCL 10MG

PURPOSE

Antihistamine

Do not use

if you have ever had an allergic reaction to this product or any of its ingredients or to an antihistamine containing hydroxyzine.

Ask a doctor before use if you have

liver or kidney disease. Your doctor should determine if you need a different dose.

Ask a doctor or pharmacist before use if you are

taking tranquilizers or sedatives.

When using this product

•
drowsiness may occur
•
avoid alcoholic drinks
•
alcohol, sedatives, and tranquilizers may increase drowsiness
•
be careful when driving a motor vehicle or operating machinery

Stop use and ask a doctor if

an allergic reaction to this product occurs. Seek medical help right away.

If pregnant or breast-feeding:

•
if breast-feeding: not recommended
•
if pregnant: ask a health professional before use.

Keep out of reach of children.

In case of overdose, get medical help or contact a Poison Control Center right away. (1-800-222-1222)

INACTIVE INGREDIENT

corn starch, FD&C blue no. 1 aluminum lake, hypromellose, lactose monohydrate, magnesium stearate, polydextrose, polyethylene glycol, povidone, titanium dioxide, triacetin

Keep out of reach of children.

In case of overdose, get medical help or contact a Poison Control Center right away. (1-800-222-1222)